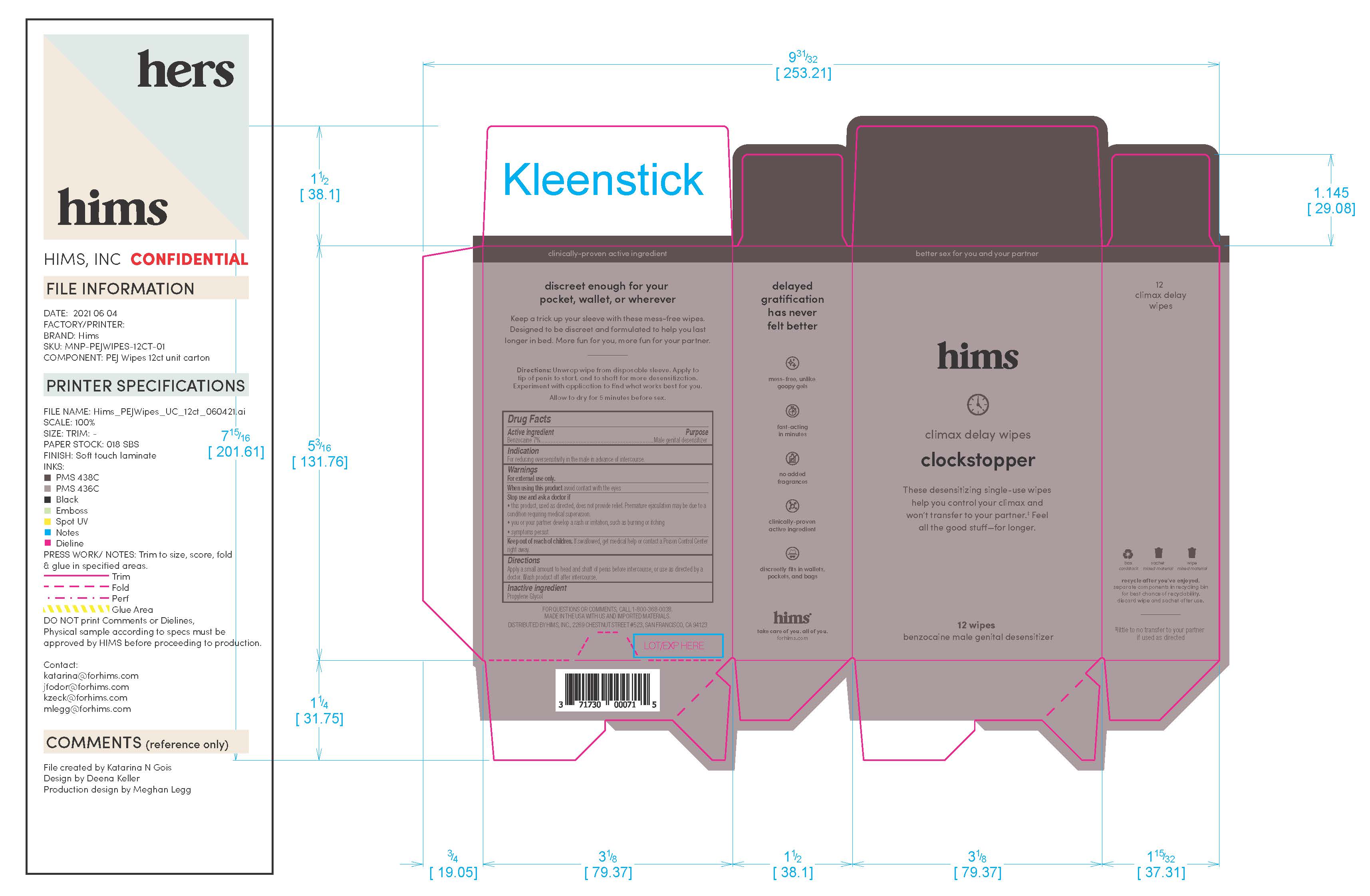 DRUG LABEL: Hims Delay Wipes
NDC: 71730-009 | Form: DRESSING
Manufacturer: Hims Inc.
Category: otc | Type: HUMAN OTC DRUG LABEL
Date: 20231107

ACTIVE INGREDIENTS: BENZOCAINE 70 g/1000 g
INACTIVE INGREDIENTS: PROPYLENE GLYCOL

Hims Delay Wipes

Warnings

For external use only

When using this prouct avoid contact with the eyes

Stop and ask doctor if: the product, used as directed, does not provide relief. Premature ejaculation may be due to a condition requiring medical supervision. You or your partner develop a rash or irritation, such as burning or itching. If symptoms persist.

If swallowed, get medical help or contact a Poison Control Center right away.

Directions

Apply a small amount to head and shaft of penis before intercourse, or use as directed by a doctor. Wash product off after intercourse.

Indications

For reducing oversensitivity in the male in advance of intercourse.

Indications

For reducing oversensitivity in the male in advance of intercourse.

Active Ingredient

Benzocaine 7% Male Genital Desensitizer

Inactive Ingredient

Propylene glycol

Keep out of reach of children

Quesitons?

For questions or comments call 1-800-368-0038

Other Information

Made in the USA with US and imported materials.

Distributed by HIMS, Inc., 2269 Chestnut Street #523, San Francisco, CA 94123